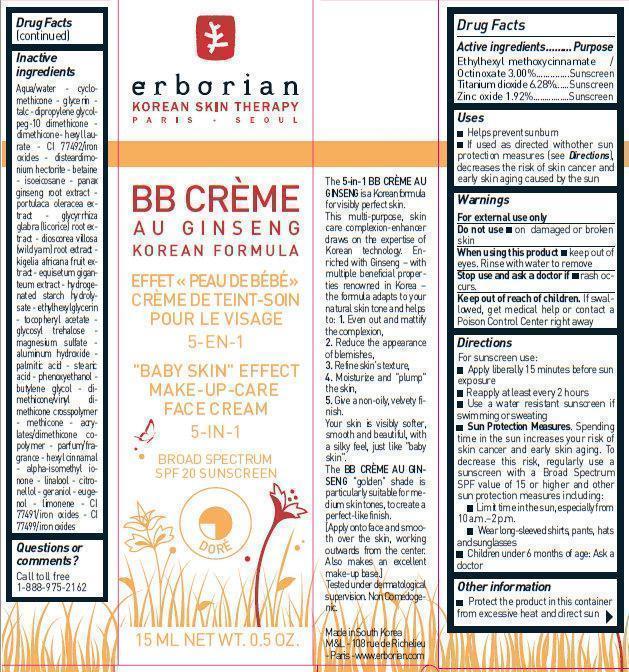 DRUG LABEL: ERBORIAN - BB CREME AU GINSENG DORE SPF 20
NDC: 10345-901 | Form: CREAM
Manufacturer: LABORATOIRES M&L
Category: otc | Type: HUMAN OTC DRUG LABEL
Date: 20241211

ACTIVE INGREDIENTS: OCTINOXATE 30 mg/1 mL; TITANIUM DIOXIDE 62.8 mg/1 mL; ZINC OXIDE 19.2 mg/1 mL
INACTIVE INGREDIENTS: WATER; CYCLOMETHICONE; GLYCERIN; DIPROPYLENE GLYCOL; DIMETHICONE; HEXYL LAURATE; FERRIC OXIDE YELLOW; DISTEARDIMONIUM HECTORITE; BETAINE; ISOEICOSANE; ASIAN GINSENG; PURSLANE; LICORICE; DIOSCOREA VILLOSA TUBER; KIGELIA AFRICANA FRUIT; ETHYLHEXYLGLYCERIN; .ALPHA.-TOCOPHEROL ACETATE; MAGNESIUM SULFATE, UNSPECIFIED FORM; ALUMINUM HYDROXIDE; PALMITIC ACID; STEARIC ACID; PHENOXYETHANOL; BUTYLENE GLYCOL; .ALPHA.-HEXYLCINNAMALDEHYDE; ISOMETHYL-.ALPHA.-IONONE; LINALOOL, (+/-)-; .BETA.-CITRONELLOL, (R)-; GERANIOL; EUGENOL; FERRIC OXIDE RED; FERROSOFERRIC OXIDE

ERBORIAN - BB CREME AU GINSENG DORE SPF 20

Active ingredients

Ethylhexyl methoxycinnamate / Octinoxate 3.00%....….......Sunscreen
Titanium dioxide 6.28%......Sunscreen
Zinc oxide 1.92%................Sunscreen

Purpose

Sunscreen

Uses

- Helps prevent sunburn
- If used as directed with other sun protection measures (see Directions), decreases the risk of skin cancer and early skin aging caused by the sun

Warnings

For external use only

Do not use

- on damaged or broken skin

When using this product

- keep out of eyes. Rinse with water to remove

Stop use and ask a doctor if

rash occurs.

Keep out of reach of children.

If swallowed, get medical help or contact a Poison Control Center right away

Directions

For sunscreen use:

- Apply liberally 15 minutes before sun exposure
- Reapply at least every 2 hours
- Use a water resistant sunscreen if swimming or sweating
- Sun Protection Measures. Spending time in the sun increases your risk of skin cancer and early skin aging. To decrease this risk, regularly use a sunscreen with a Broad Spectrum SPF value of 15 or higher and other sun protection measures including:
- Limit time in the sun, especially from 10 a.m. –2 p.m.
- Wear long-sleeved shirts, pants, hats and sunglasses
- Children under 6 months of age: Ask a doctor

Other information

- Protect the product in this container from excessive heat and direct sun

Inactive ingredients

Aqua/water - cyclomethicone - glycerin - talc - dipropylene glycolpeg-10 dimethicone - dimethicone - hexyl laurate - CI 77492/iron oxides - disteardimonium hectorite - betaine - isoeicosane - panax ginseng root extract - portulaca oleracea extract - glycyrrhiza glabra (licorice) root extract - dioscorea villosa (wild yam) root extract - kigelia africana fruit extract - equisetum giganteum extract - hydrogenated starch hydrolysate - ethylhexylglycerin - tocopheryl acetate - glycosyl trehalose - magnesium sulfate - aluminum hydroxide - palmitic acid - stearic
acid - phenoxyethanol - butylene glycol - dimethicone/vinyl dimethicone crosspolymer - methicone - acrylates/dimethicone copolymer - parfum/fragrance - hexyl cinnamal - alpha-isomethyl ionone - linalool - citronellol - geraniol - eugenol - limonene - CI 77491/iron oxide

Questions or comments?

Call toll free 1-888-975-2162